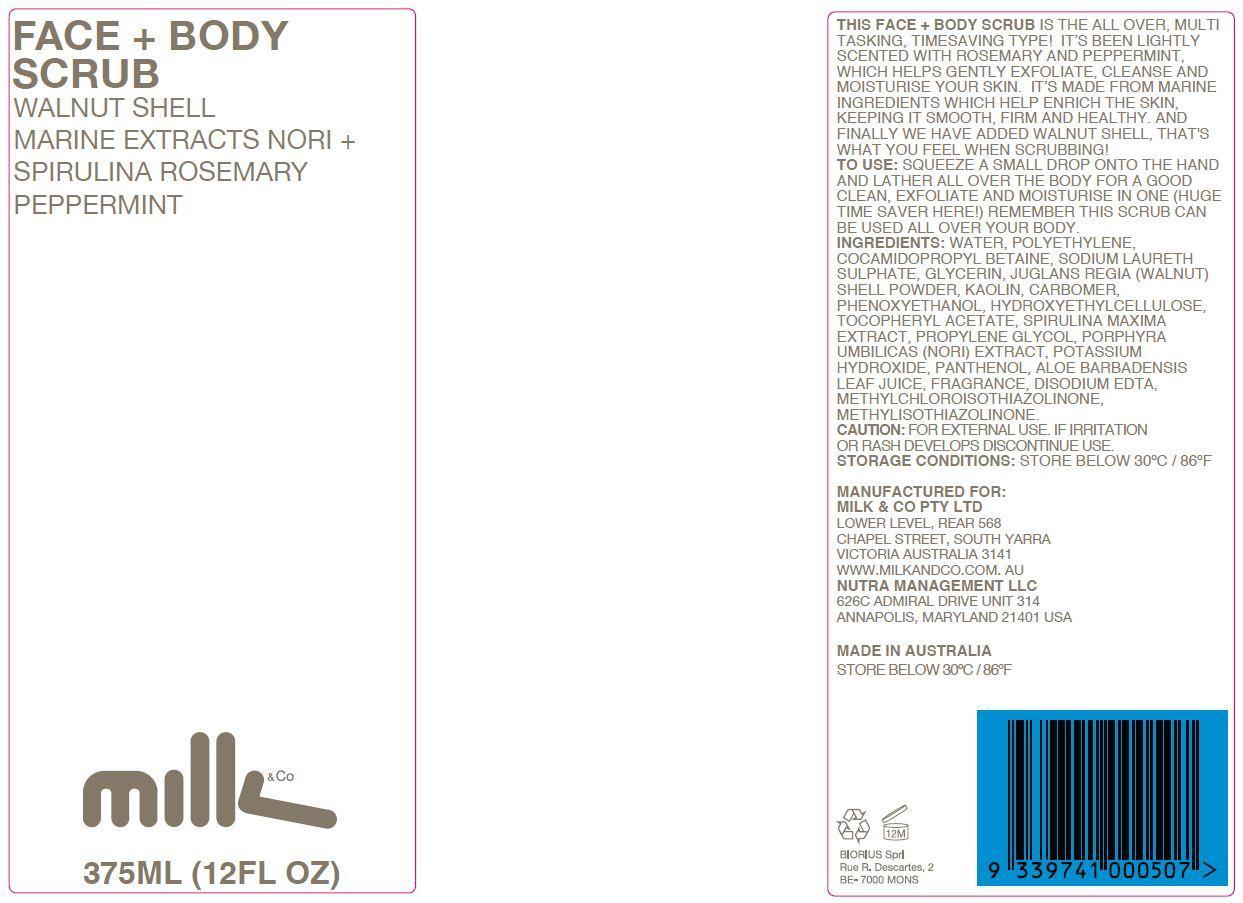 DRUG LABEL: Body Scrub
NDC: 61671-003 | Form: GEL
Manufacturer: Milk & Co Pty Ltd
Category: otc | Type: HUMAN OTC DRUG LABEL
Date: 20140108

ACTIVE INGREDIENTS: GLYCERIN 7.5 g/375 g; KAOLIN 6 g/375 g
INACTIVE INGREDIENTS: ALOE VERA LEAF; COCAMIDOPROPYL BETAINE; EDETATE DISODIUM; CARBOMER HOMOPOLYMER TYPE C (ALLYL PENTAERYTHRITOL CROSSLINKED); HYDROXYETHYL CELLULOSE (100 MPA.S AT 2%); JUGLANS REGIA SHELL; METHYLCHLOROISOTHIAZOLINONE; METHYLISOTHIAZOLINONE; PANTHENOL; PHENOXYETHANOL; HIGH DENSITY POLYETHYLENE; PORPHYRA UMBILICALIS; WATER; POTASSIUM HYDROXIDE; PROPYLENE GLYCOL; SODIUM LAURETH SULFATE; SPIRULINA MAXIMA; .ALPHA.-TOCOPHEROL ACETATE

ACTIVE INGREDIENT

Glycerin and Kaolin

PURPOSE

Face + Body Scrub

Walnut Shell

Marine Extracts Nori + Spirulina Rosemary Peppermint

Milk & Co

375 ML (12 FL OZ)

Keep out of reach of children.

INDICATIONS AND USAGE

This Face + Body Scrub is the all over, multi tasking, timesaving type! It's been lightly scented with rosemary and peppermint, which helps gently exfoliate, cleanse, and moisturise your skin. It's made from marine ingredients which help enrich the skin, keeping it smooth, firm, and healthy. And finally we have added walnut shell, that's what you feel when scrubbing!

WARNINGS

Caution: for external use. If irritation or rash develops discontinue use.

Storage conditions: store belowe 30oC / 86oF

DOSAGE AND ADMINISTRATION

To use: Squeeze a small drop onto the hand and lather all over the body for a good clean, exfoliate and moisturise in one (huge time saver here!) remember this scrub can be used all over your body.

INACTIVE INGREDIENT

Ingredients: water, polyethylene, cocamidopropyl betaine, sodium laureth sulphate, glycerin, juglans regia (walnut) shell powder, kaolin, carbomer, phenoxyethanol, hydroxyethylcellulose, tocopheryl acetate, spirulina maxima extract, propylene glycol, porphyra umbilicas (nori) extract, potassium hydroxide, panthenol, aloe barbadensis leaf juice, fragrance, disodium EDTA, methylchloroisothiazolinone, methylisothiazolinone.

OTHER SAFETY INFORMATION

Manufactured for:

Milk & Co Pty Ltd

Lower level, rear 568

Chapel Street, South Yarra

Victoria, Australia 3141

www.milkandco.com.au

Nutra Management LLC

626C Admiral Drive Unit 314

Annapolis, Maryland 21041 USA

Made in Australia